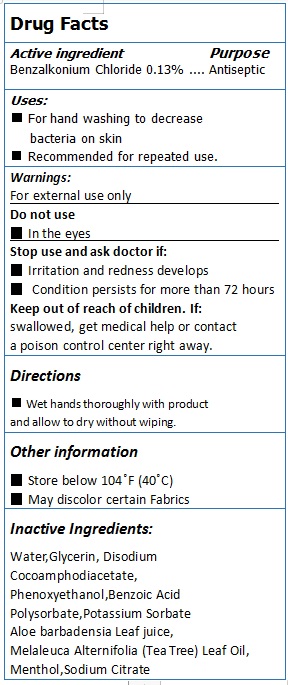 DRUG LABEL: ANTISEPTIC SANITIZING WIPES
NDC: 79294-001 | Form: CLOTH
Manufacturer: HANGZHOU WIPEX NONWOVENS CO., LTD.
Category: otc | Type: HUMAN OTC DRUG LABEL
Date: 20200729

ACTIVE INGREDIENTS: BENZALKONIUM CHLORIDE 0.13 g/100 g
INACTIVE INGREDIENTS: WATER; ALOE VERA LEAF; GLYCERIN; POTASSIUM SORBATE; BENZOIC ACID; POLYSORBATE 20; PHENOXYETHANOL; DISODIUM COCOAMPHODIACETATE; MENTHOL; TEA TREE OIL; SODIUM CITRATE

79294-001 ANTISEPTIC SANITIZING WIPES 0.13% BENZALKONIUM CHLORIDE

Active Ingredient

Benzalkonium Chloride 0.13%

Purpose

Antiseptic

USE

Use for hand sanitizing to decrease bacteria on the skin
recommended for repeated use.

Warning

For external use only
DO not use
In the eyes
Stop use and ask doctor if:
Irritation and redness develops
Condition persists for more than 72 hours

Keep out of reach of children. If:
swallowed, get medical help or contact
a poison control center right away.

Directions

Wet hands thoroughly with product
and allow to dry without wiping.

Inactive ingredients

Water,Glycerin, Disodium
Cocoamphodiacetate,
Phenoxyethanol,Benzoic Acid
Polysorbate,Potassium Sorbate
Aloe barbadensia Leaf juice,
Melaleuca Alternifolia (Tea Tree) Leaf Oil,
Menthol, Sodium Citrate